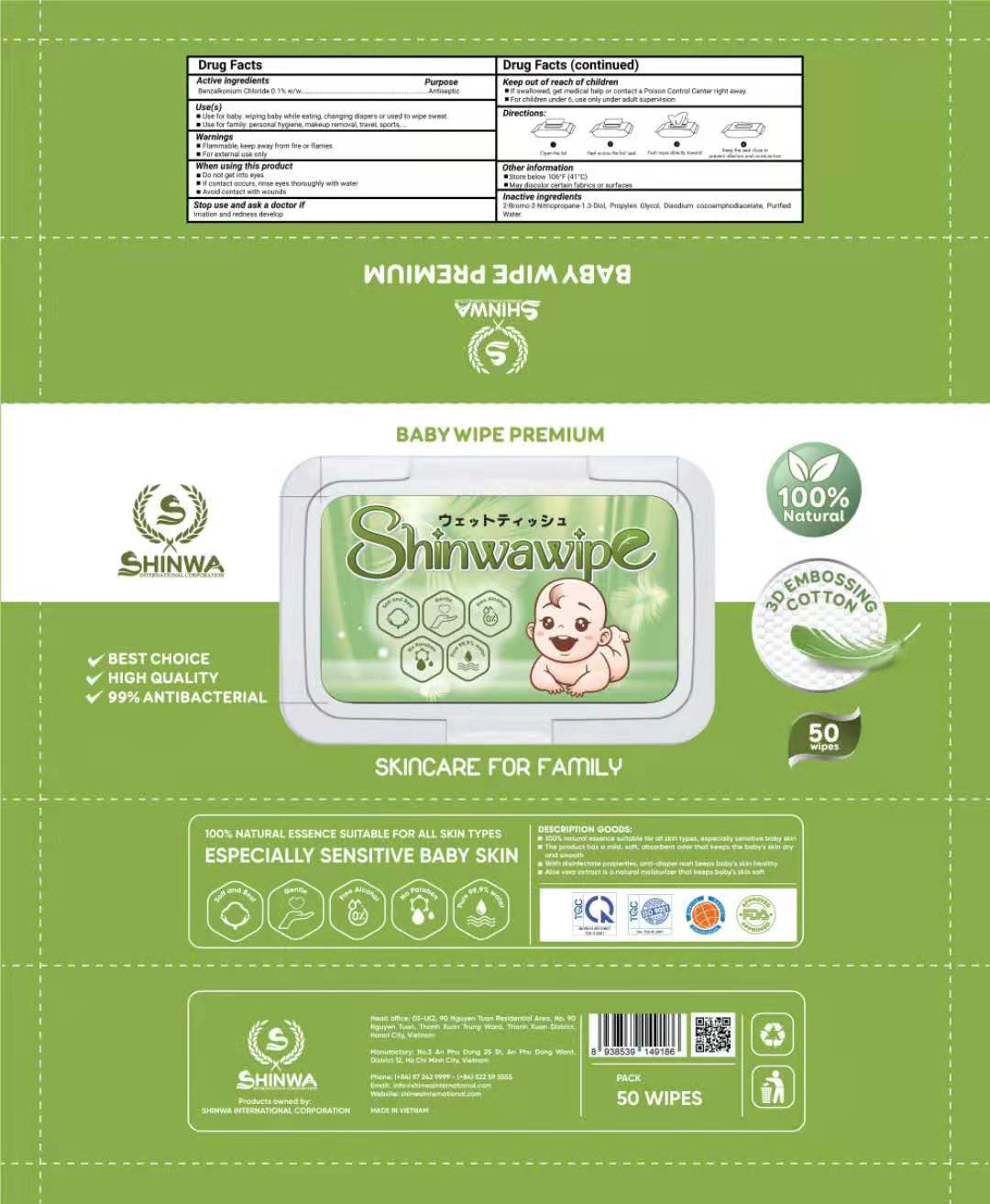 DRUG LABEL: BABY WIPE PREMIUM
NDC: 81889-501 | Form: CLOTH
Manufacturer: SHINWA INTERNATIONAL CORPORATION
Category: otc | Type: HUMAN OTC DRUG LABEL
Date: 20210513

ACTIVE INGREDIENTS: BENZALKONIUM CHLORIDE 0.1 1/100 1
INACTIVE INGREDIENTS: DISODIUM COCOAMPHODIACETATE; BRONOPOL; PROPYLENE GLYCOL; WATER; ALOE VERA LEAF

BABY WIPE PREMIUM

BABY WIPE PREMIUM

Active Ingredient(s)

BENZALKONIUM CHLORIDE 0.1% w/w, Antiseptic

Purpose

Antiseptic, BABY WIPE PREMIUM

Use

BABY WIPE PREMIUM to help reduce bacteria that potentially can cause disease. For use when soap and water are not available.

Warnings

For external use only.

Do not use

- on open skin wounds

When using this product keep out of eyes, ears, and mouth. In case of contact with eyes, rinse eyes thoroughly with water.
Stop use and ask a doctor if irritation or rash occurs. These may be signs of a serious condition.
Keep out of reach of children. If swallowed, get medical help or contact a Poison Control Center right away.

Stop use and ask a doctor if irritation or rash occurs. These may be signs of a serious condition.

Keep out of reach of children. If swallowed, get medical help or contact a Poison Control Center right away.

Directions

- Wipe the skin and let it dry naturally.
- Supervise children under 6 years of age when using this product to avoid swallowing.

Other information

- Store between 15-30C (59-86F)
- Avoid freezing and excessive heat above 40C (104F)

Inactive ingredients

PURIFIED WATER
PROPYLEN GLYCOL
DISODIUM COCOAMPHODIACETATE
2-BROMO-2-NITROPROPANE 1.3-DIOL